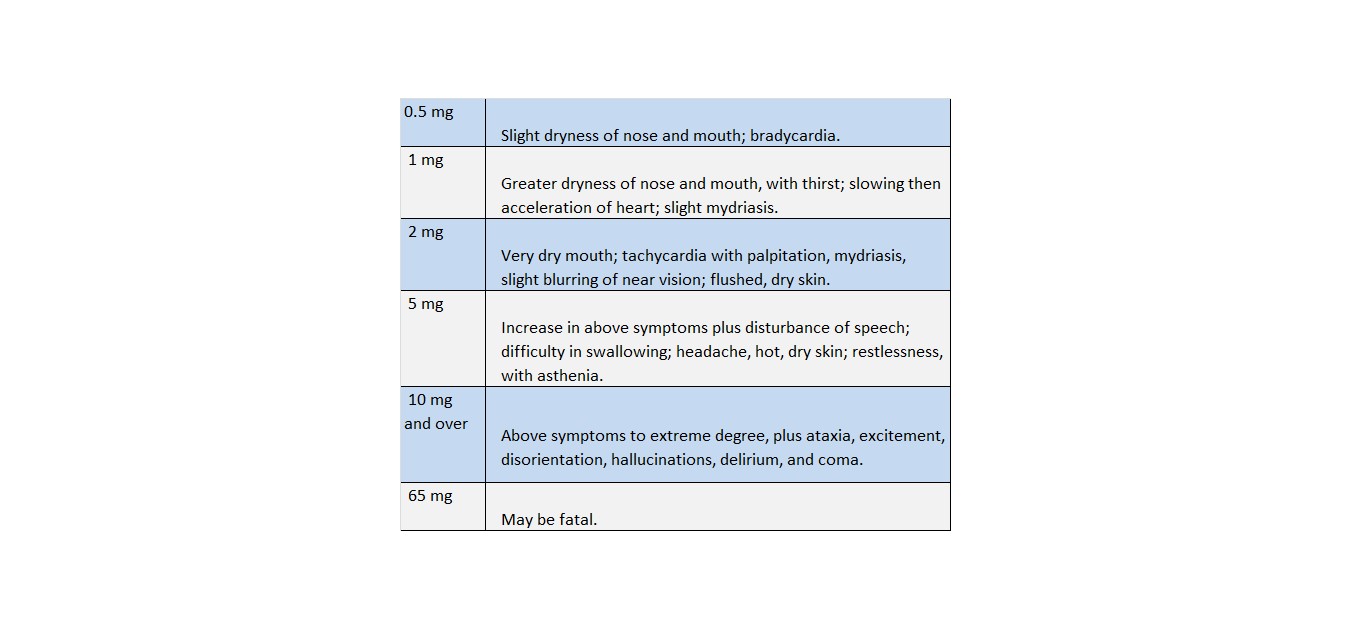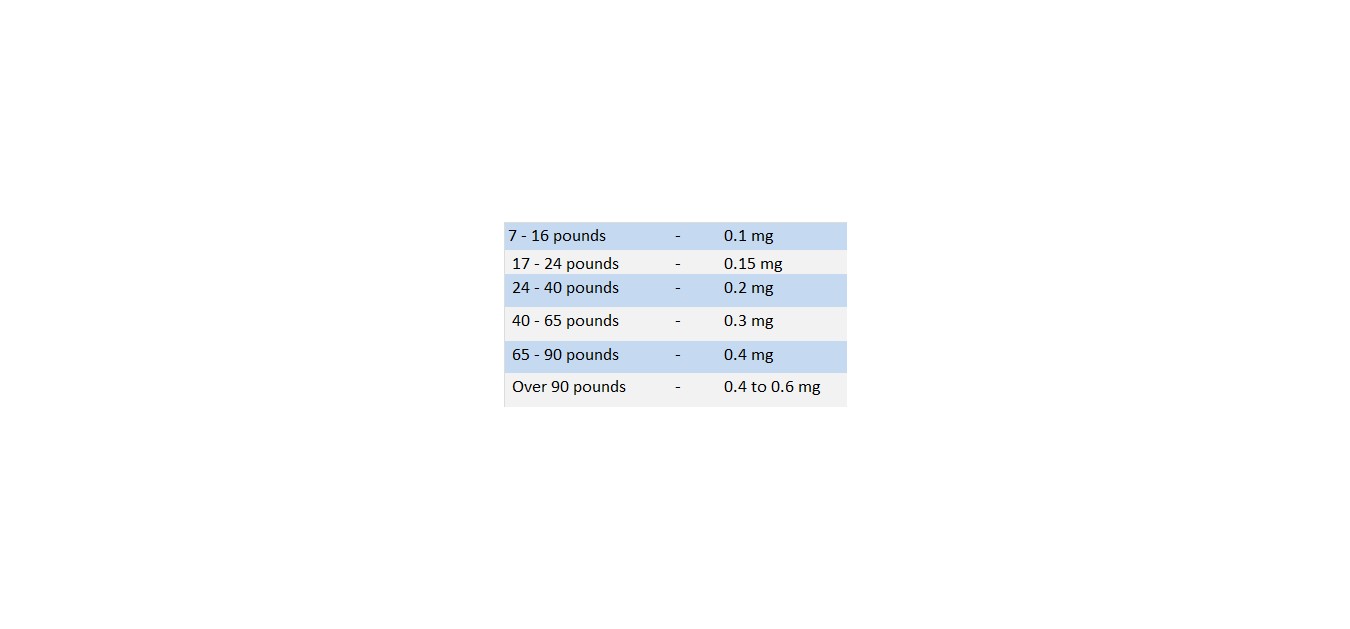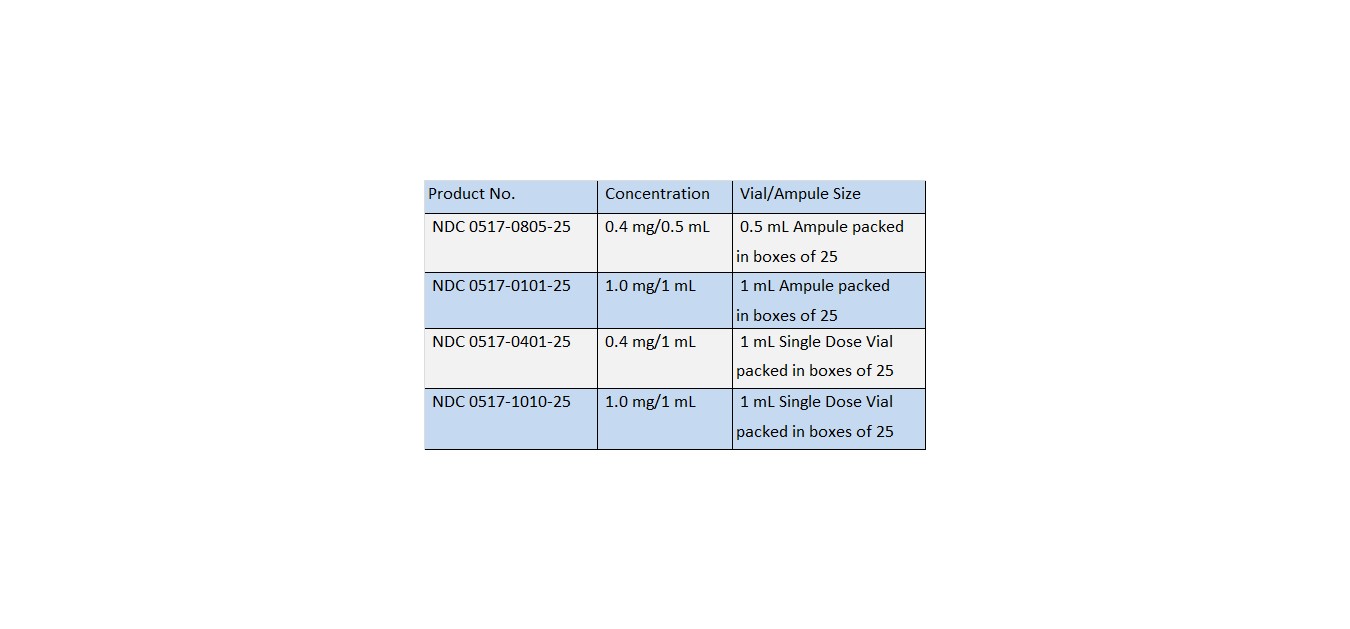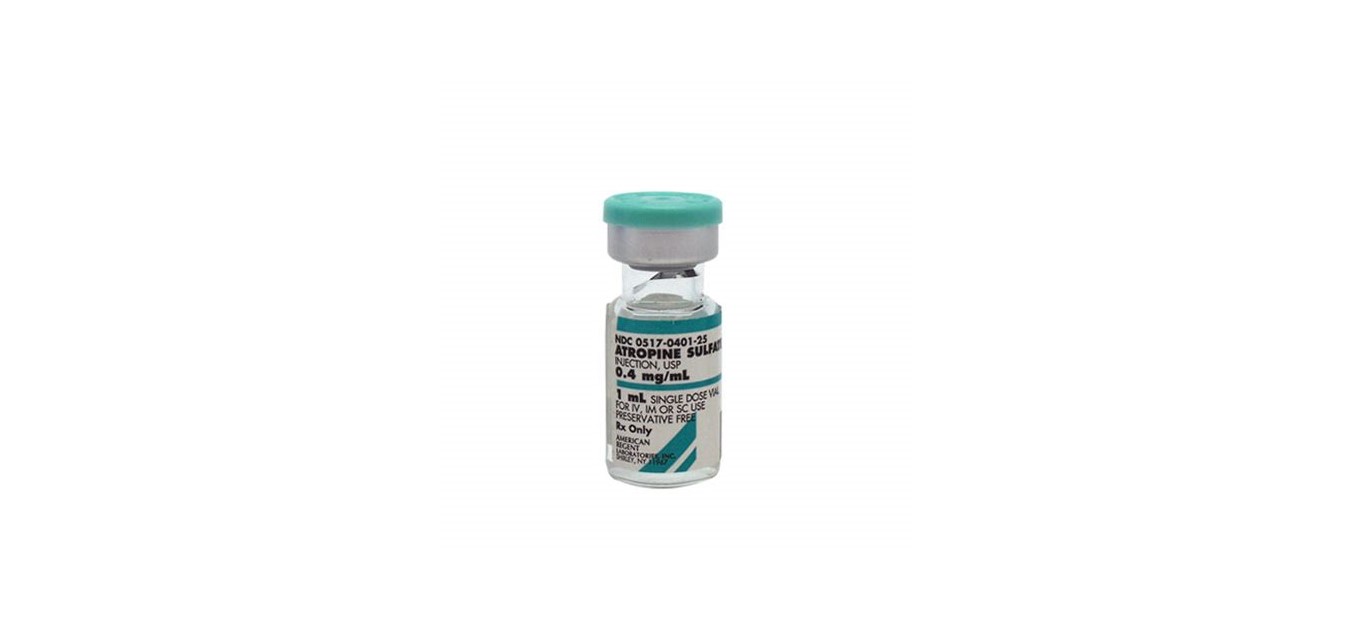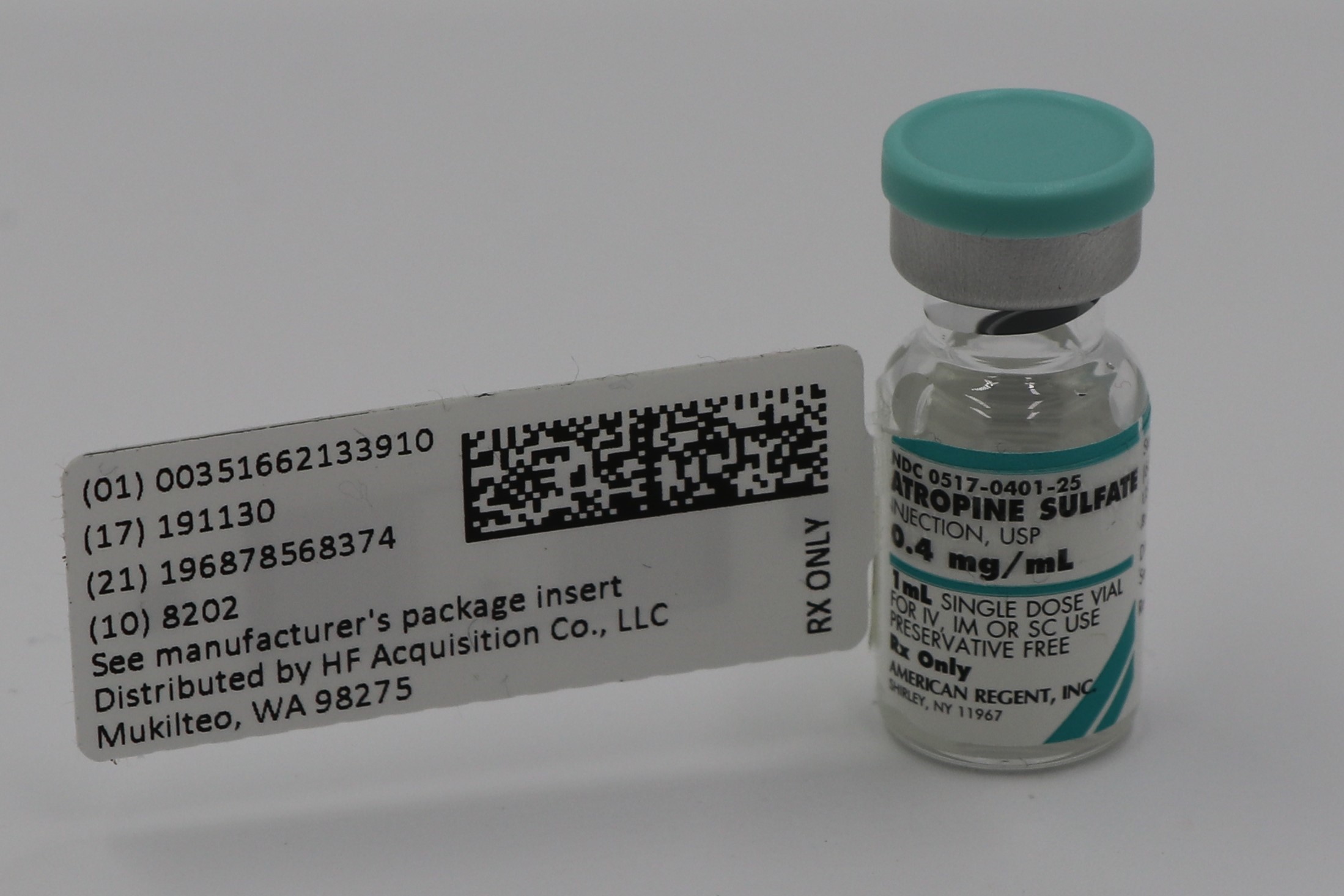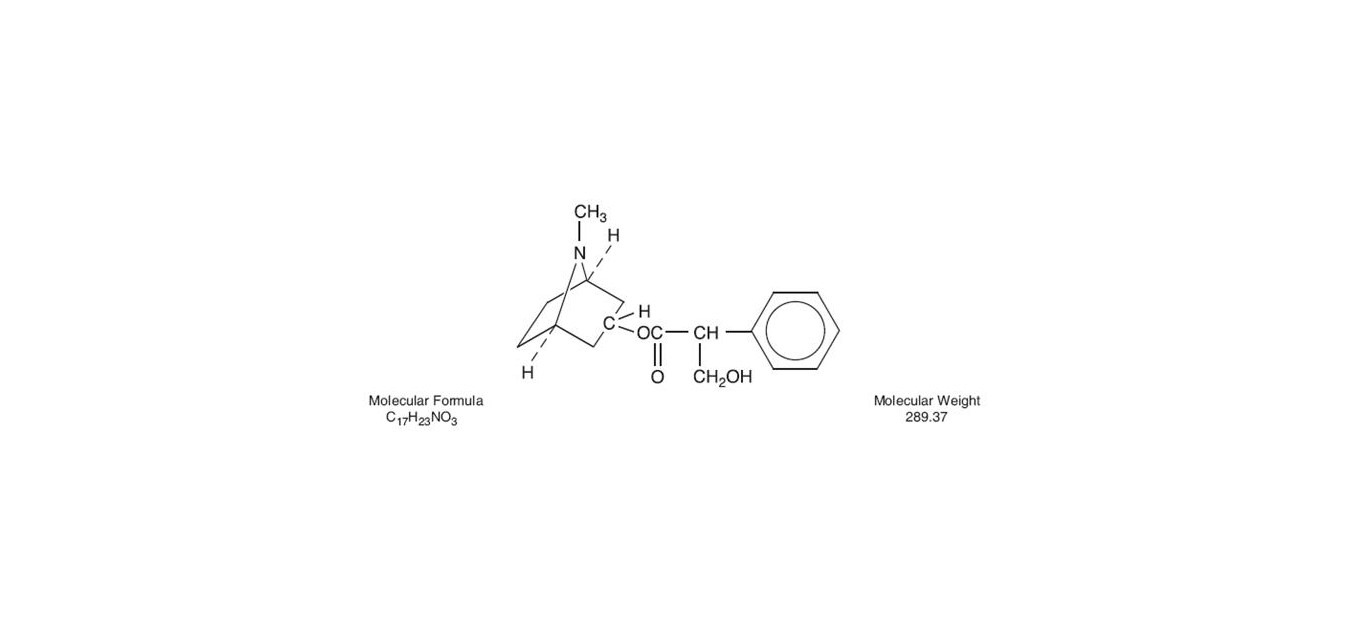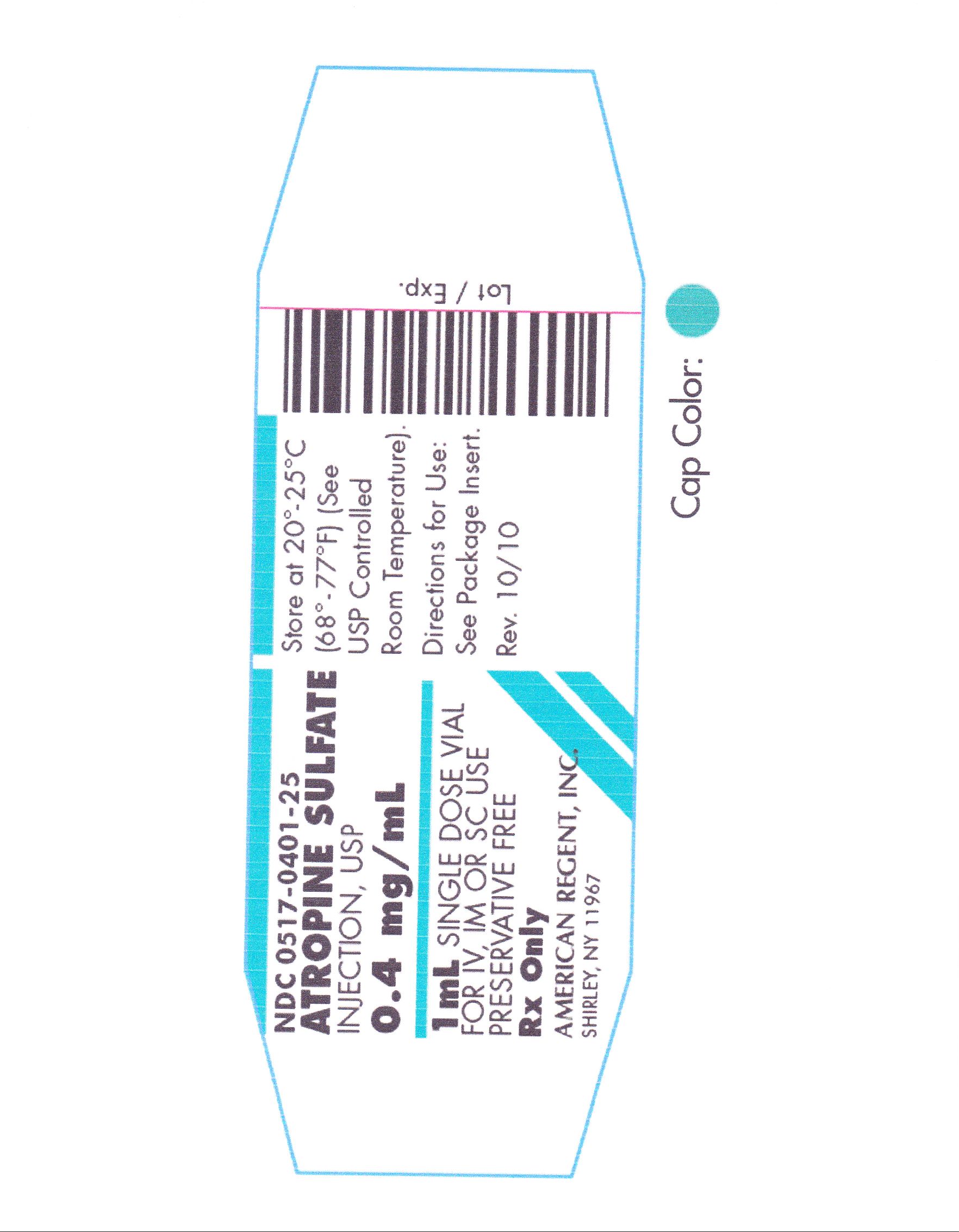 DRUG LABEL: ATROPINE SULFATE
NDC: 51662-1339 | Form: INJECTION, SOLUTION
Manufacturer: HF Acquisition Co LLC, DBA HealthFirst
Category: prescription | Type: HUMAN PRESCRIPTION DRUG LABEL
Date: 20221209

ACTIVE INGREDIENTS: ATROPINE SULFATE 0.4 mg/1 mL
INACTIVE INGREDIENTS: WATER; SODIUM CHLORIDE 9 mg/1 mL; SULFURIC ACID

ATROPINE SULFATE INJECTION, USP 0.4mg/mL 1mL VIAL

SPL UNCLASSIFIED

Rx Only

(pH 3.0 - 6.5)

DESCRIPTION

Atropine Sulfate Injection, USP is a sterile, isotonic solution of Atropine Sulfate in Water for Injection q.s. Sodium Chloride added for isotonicity. pH adjusted with Sulfuric Acid. Preservative free.

Atropine is a white crystalline alkaloid which may be extracted from belladonna root and hyoscyamine or may be produced synthetically. It is used in the form of atropine sulfate because this compound has much greater solubility in water. The structural formula of Atropine is as follows:

CLINICAL PHARMACOLOGY

Atropine has two actions. The most important therapeutic action is the inhibition of smooth muscle and glands innervated by postganglionic cholinergic nerves. Atropine also has central-nervous system activity, which may be stimulating or depressing depending upon the dose.

INDICATIONS & USAGE

1. In the treatment of parkinsonism. Rigidity and tremor relieved by the apparently selective depressant action.
2. In the gastrointestinal tract to relieve pylorospasm, hypertonicity of the small intestine and the hypermotility of the colon.
3. To relieve hypertonicity of the uterine muscle.
4. To relax the spasm of biliary and uretered colic and bronchial spasm.
5. To diminish the tone of the detrusor muscle of the urinary bladder in the treatment of urinary tract disorders.
6. To control the crying and laughing episodes in patients with brain lesions.
7. In cases of closed head injuries which cause acetylcholine to be released or to be present in cerebrospinal fluid which in turn causes abnormal EEG patterns, stupor and neurological signs.
8. In the management of peptic ulcer.
9. In anesthesia to control excessive salivation and bronchial secretions.
10. To control rhinorrhea of acute rhinitis or hay fever.
11. As an antidote for pilocarpine, physostigmine, isoflurophate, choline esters, certain species of Aminata and in cases of anticholinesterase insecticide poisoning.
12. In poisoning by the organic phosphate cholinesterase inhibitors found in certain insecticides and by chemical warfare “nerve gases”, large doses of atropine relieve the muscarine-like symptoms and some of the central-nervous-system manifestations. Adults suspected of contact with organic phosphorus insecticides of the parathion type should be given atropine sulfate, 0.8 mg, intramuscularly. If an atropine effect is not apparent within thirty minutes or if definite symptoms of the poisoning occur (nausea, vomiting, diarrhea, pupillary constriction, pulmonary edema, fasciculations of eyelids and tongue, jerky ocular movements, and excessive sweating, salivation, and bronchial secretion), atropine sulfate, 2 mg, should be given intramuscularly at hourly intervals until signs of atropinization are observed. Up to two or three times this dose (4 to 6 mg) may be required in severe cases. Removing contaminated clothing, washing the skin, and commencing artificial respiration and supportive therapy are also indicated.

CONTRAINDICATIONS

Conditions in which inhibition of postganglionic cholinergic nerves are undesirable, such as glaucoma and tachycardia. Also contraindicated in asthma, because the parenteral dose which might relieve asthma would have an excessive drying effect upon mucous plugs in the bronchi. Prostatic hypertrophy, while not a contraindication, requires special attention to signs of urinary retention.

WARNINGS

This drug is effective in very low dosage and overdose may cause permanent damage or death, especially in children.

WARNINGS

Doses of 0.5 to 1 mg of atropine are mildly stimulating to the central nervous system. Larger doses may produce mental disturbances; still larger doses are depressing. Death from atropine poisoning, though rare, is usually due to paralysis of the medullary centers.

Pregnancy

Teratogenic Effects

Pregnancy Category B. Reproduction studies have been performed in mice in doses of 50 mg/kg of body weight and have revealed no evidence of impaired fertility or harm to the fetus due to Atropine Sulfate. There are, however, no adequate and well-controlled studies in pregnant women. Because animal reproduction studies are not always predictive of human response, this drug should be used during pregnancy only if clearly needed.

ADVERSE REACTIONS

Toxic effects from overdosage of atropine are not uncommon, especially in children. Individual tolerance varies greatly, but these systemic doses are likely to produce the following effects.

A scarlatiniform rash may occur. Atropine may produce fever, particularly in children, through inhibition of heat loss by evaporation. Although large doses of atropine may cause an alarming condition, recovery is usual.

In the treatment of atropine poisoning, respiratory assistance and symptomatic support are indicated.

Pilocarpine is sometimes given but is of limited value.

OVERDOSAGE

1. If marked excitement is present, a short acting barbiturate, chloral hydrate of paraldehyde may be used for sedation. Large doses should be avoided if possible and must be carefully controlled so that they will not add to the depressive stages of atropine poisoning.
2. Artificial respiration with oxygen is necessary when respiration is depressed.
3. Depression may be controlled by use of caffeine, sodium benzoate or picrotoxin together with the inhalation of oxygen.
4. As a physiologic antidote, neostigmine methylsulfate may be given by intramuscular injection in doses of 500 mcg to 1 mg and repeated every 2 to 9 hours.
5. Remaining therapy is purely symptomatic. Icebags and alcohol sponges help to reduce fever, especially in children. Careful nursing is essential. The room should be darkened, because of the patient’s marked photophobia.

DOSAGE & ADMINISTRATION

The usual adult dose of atropine is 0.4 to 0.6 mg. Suggested doses for children are as follows:

As indicated previously, however, these doses may be considerably exceeded in certain cases.

Parenteral drug products should be inspected visually for particulate matter and discoloration, whenever solution and container permit.

HOW SUPPLIED

ATROPINE SULFATE INJECTION, USP is supplied in the following dosage forms.
NDC 51662-1339-1
ATROPINE SULFATE INJECTION, USP 0.4mg/mL 1mL VIAL

HF Acquisition Co LLC, DBA HealthFirst
Mukilteo, WA 98275

Also supplied in the following manufacture supplied dosage forms

Store at 20° to 25°C (68° to 77°F); excursions permitted to 15° to 30°C (59° to 86°F) (See USP Controlled Room Temperature).

AMERICAN
REGENT, INC.
SHIRLEY, NY 11967

IN1010
Rev. 1/09